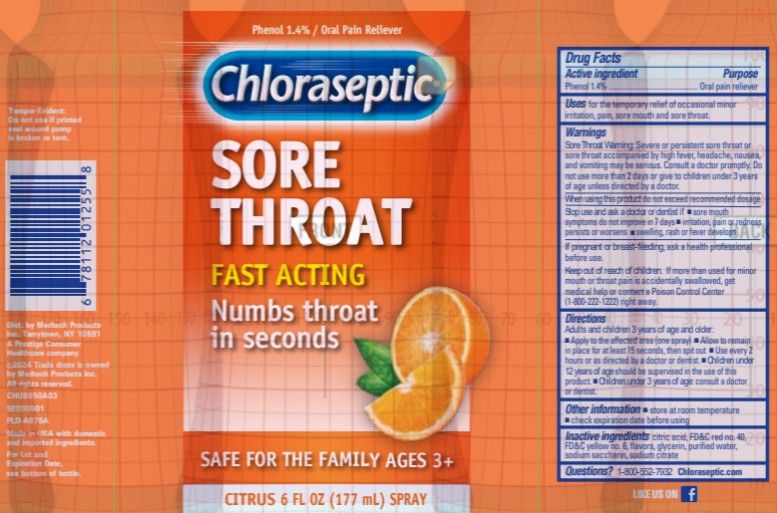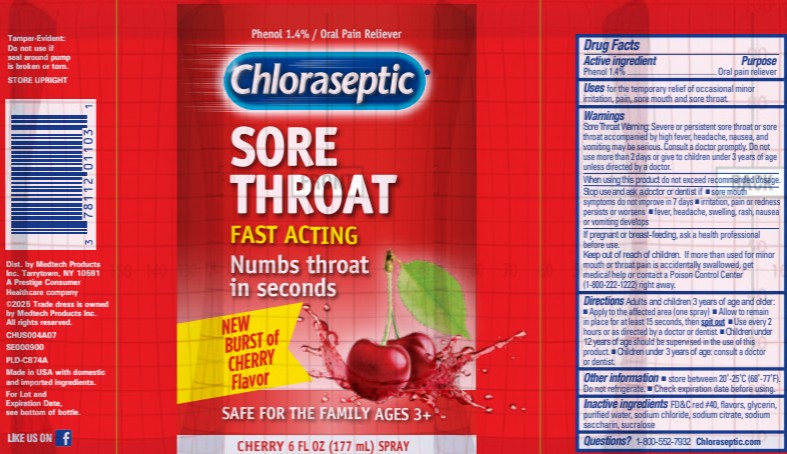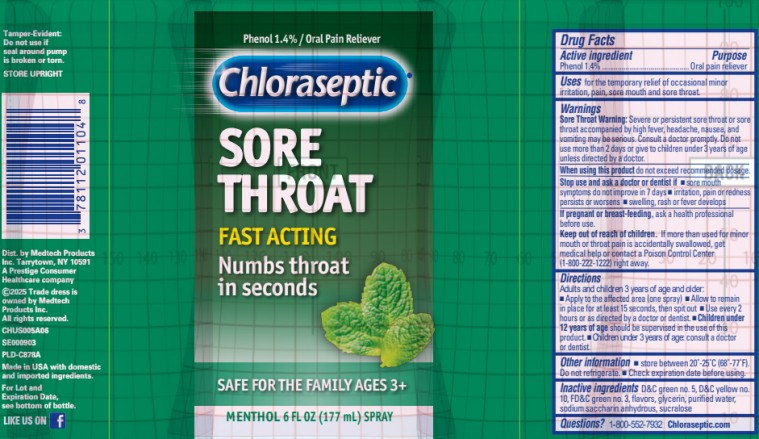 DRUG LABEL: Chloraseptic Sore Throat Citrus
NDC: 67172-112 | Form: SPRAY
Manufacturer: Prestige Brands Holdings, Inc.
Category: otc | Type: HUMAN OTC DRUG LABEL
Date: 20250926

ACTIVE INGREDIENTS: PHENOL 1.4 g/100 mL
INACTIVE INGREDIENTS: CITRIC ACID MONOHYDRATE; FD&C RED NO. 40; FD&C YELLOW NO. 6; GLYCERIN; WATER; SACCHARIN SODIUM; SODIUM CITRATE

Chloraseptic Spray

Drug Facts

Active ingredient

Phenol 1.4%

Purpose

Oral pain reliever

Uses

for the temporary relief of occasional minor irritation, pain, sore mouth and sore throat.

Warnings

Sore Throat Warning: Severe or persistent sore throat or sore throat accompanied by high fever, headache, nausea, and vomiting may be serious. Consult a doctor promptly. Do not use more than 2 days or give to children under 3 years of age unless directed by a doctor.

When using this product

do not exceed recommended dosage.

Stop use and ask a doctor or dentist if

- sore mouth symptoms do not improve in 7 days
- irritation, pain or redness persists or worsens
- swelling, rash or fever develops

If pregnant or breast-feeding,

ask a health care professional before use.

Keep out of reach of children.

If more than used for minor mouth or throat pain is accidentally swallowed, get medical help or contact a Poison Control Center (1-800-222-1222) right away.

Directions

Adults and children 3 years of age and older:

- Apply to the affected area (one spray).
- Allow to remain in place for at least 15 seconds, then spit out.
- Use every 2 hours or as directed by a doctor or dentist. Children under 12 years of age should be supervised in the use of this product. Children under 3 years of age: consult a doctor or dentist.

Other information

- store between 20-25°C (68-77 °F). Do not refrigerate.
- Check expiration date before using.

Inactive ingredients

Citric acid, FD&C Red #40, FD&C Yellow #6, flavor, glycerin, purified water, sodium saccharin, sodium citrate

Questions?

1-800-552-7932 Chloraseptic.com

Drug Facts

Active ingredient

Phenol 1.4%

Purpose

Oral pain reliever

Uses

for the temporary relief of occasional minor irritation, pain, sore mouth and sore throat.

Warnings

Sore Throat Warning: Severe or persistent sore throat or sore throat accompanied by high fever, headache, nausea, and vomiting may be serious. Consult a doctor promptly. Do not use more than 2 days or give to children under 3 years of age unless directed by a doctor.

When using this product

do not exceed recommended dosage.

Stop use and ask a doctor or dentist if

- sore mouth symptoms do not improve in 7 days
- irritation, pain or redness persists or worsens

fever, headache, swelling, rash, nausea or vomiting develops

If pregnant or breast-feeding,

ask a health care professional before use.

Keep out of reach of children.

If more than used for minor mouth or throat pain is accidentally swallowed, get medical help or contact a Poison Control Center (1-800-222-1222) right away.

Directions

Adults and children 3 years of age and older:

- Apply to the affected area (one spray).
- Allow to remain in place for at least 15 seconds, then spit out.
- Use every 2 hours or as directed by a doctor or dentist. Children under 12 years of age should be supervised in the use of this product. Children under 3 years of age: consult a doctor or dentist.

Other information

- store between 20-25°C (68-77 °F). Do not refrigerate.
- check expiration date before using.

Inactive ingredients

FD&C red no. 40, flavors, glycerin, purified water, sodium chloride, sodium citrate, sodium saccharin, sucralose

Questions?

1-800-552-7932 Chloraseptic.com

Drug Facts

Active ingredient

Phenol 1.4%

Purpose

Oral pain reliever

Uses

for the temporary relief of occasional minor irritation, pain, sore mouth and sore throat.

Warnings

Sore Throat Warning: Severe or persistent sore throat or sore throat accompanied by high fever, headache, nausea, and vomiting may be serious. Consult a doctor promptly. Do not use more than 2 days or give to children under 3 years of age unless directed by a doctor.

When using this product

do not exceed recommended dosage.

Stop use and ask a doctor or dentist if

- sore mouth symptoms do not improve in 7 days
- irritation, pain or redness persists or worsens
- swelling, rash or fever develops

If pregnant or breast-feeding,

ask a health care professional before use.

Keep out of reach of children.

If more than used for minor mouth or throat pain is accidentally swallowed, get medical help or contact a Poison Control Center (1-800-222-1222) right away.

Directions

Adults and children 3 years of age and older:

- Apply to the affected area (one spray).
- Allow to remain in place for at least 15 seconds, then spit out.
- Use every 2 hours or as directed by a doctor or dentist. Children under 12 years of age should be supervised in the use of this product. Children under 3 years of age: consult a doctor or dentist.

Other information

- store between 20-25°C (68-77 °F). Do not refrigerate.
- check expiration date before using

Inactive ingredients

D&C green no. 5, D&C yellow no. 10, FD&C green no. 3, flavor, glycerin, purified water, sodium saccharin, sucralose

Questions?

1-800-552-7932 Chloraseptic.com

PRINCIPAL DISPLAY PANEL

Chloraseptic®
Phenol/Oral Anesthetic
CITRUS
6 FL OZ (177 mL)

PRINCIPAL DISPLAY PANEL

Chloraseptic® Phenol/Oral Anesthetic
CHERRY Flavor

6 FL OZ (177 mL)

PRINCIPAL DISPLAY PANEL

Chloraseptic® Phenol/Oral Anesthetic
MENTHOL Flavor| 6 FL OZ (177 mL)